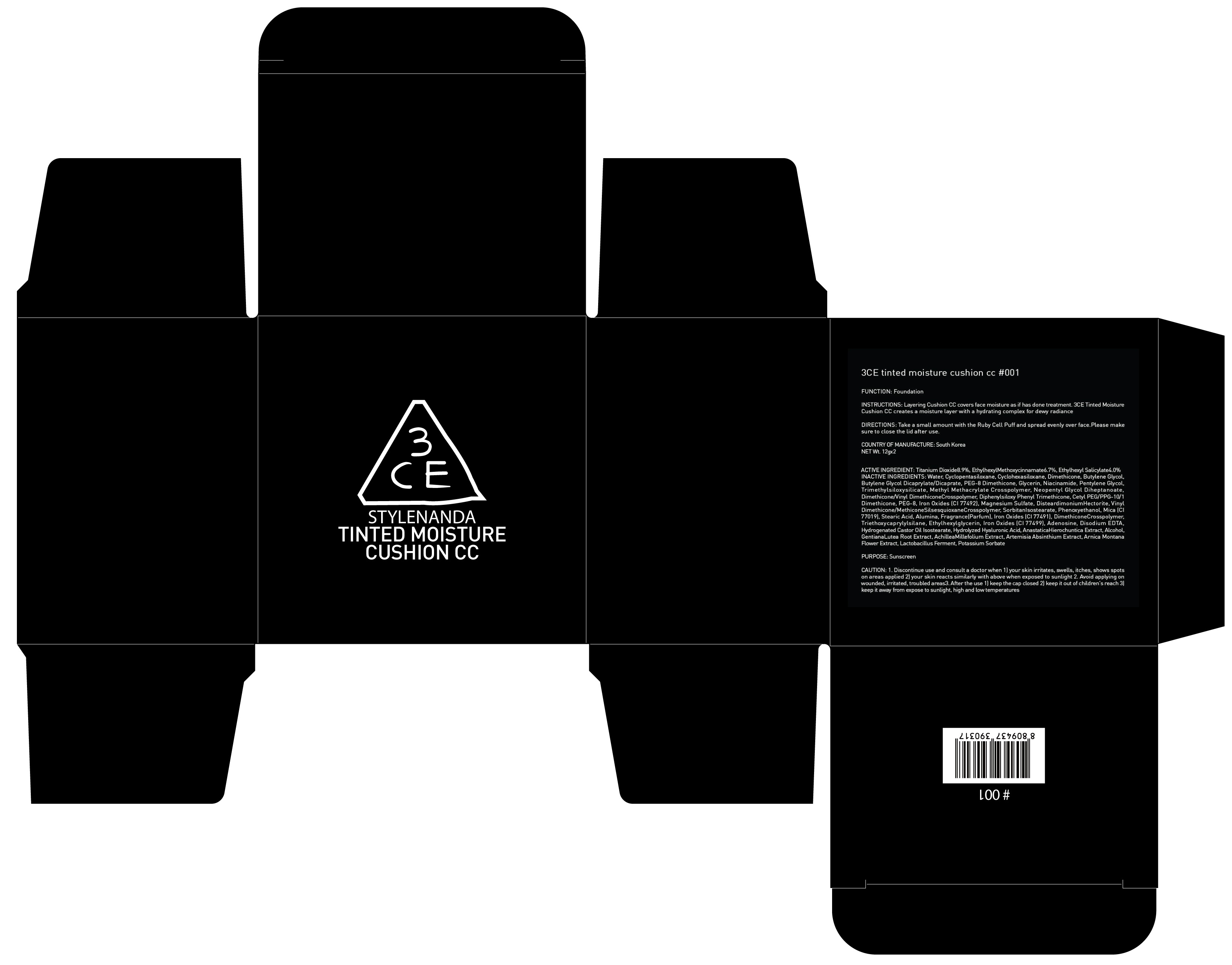 DRUG LABEL: 3CE Tinted moisture cushion CC 001
NDC: 60764-129 | Form: POWDER
Manufacturer: Nanda Co., Ltd
Category: otc | Type: HUMAN OTC DRUG LABEL
Date: 20161017

ACTIVE INGREDIENTS: Titanium Dioxide 1.06 g/12 g; Octinoxate 0.80 g/12 g; Octisalate 0.48 g/12 g
INACTIVE INGREDIENTS: Water; Dimethicone

ACTIVE INGREDIENT

Active Ingredient: Titanium Dioxide 8.9%, Ethylhexyl Methoxycinnamate 6.7%, Ethylhexyl Salicylate 4.0%

INACTIVE INGREDIENT

Inactive Ingredients: Water, Cyclopentasiloxane, Cyclohexasiloxane, Dimethicone, Butylene Glycol, Butylene Glycol Dicaprylate/Dicaprate, PEG-8 Dimethicone, Glycerin, Niacinamide, Pentylene Glycol, Trimethylsiloxysilicate, Methyl Methacrylate Crosspolymer, Neopentyl Glycol Diheptanoate, Dimethicone/Vinyl DimethiconeCrosspolymer, Diphenylsiloxy Phenyl Trimethicone, Cetyl PEG/PPG-10/1 Dimethicone, PEG-8, Iron Oxides (CI 77492), Magnesium Sulfate, DisteardimoniumHectorite, Vinyl Dimethicone/MethiconeSilsesquioxaneCrosspolymer, SorbitanIsostearate, Phenoxyethanol, Mica (CI 77019), Stearic Acid, Alumina, Fragrance(Parfum), Iron Oxides (CI 77491), DimethiconeCrosspolymer, Triethoxycaprylylsilane, Ethylhexylglycerin, Iron Oxides (CI 77499), Adenosine, Disodium EDTA, Hydrogenated Castor Oil Isostearate, Hydrolyzed Hyaluronic Acid, AnastaticaHierochuntica Extract, Alcohol, GentianaLutea Root Extract, AchilleaMillefolium Extract, Artemisia Absinthium Extract, Arnica Montana Flower Extract, Lactobacillus Ferment, Potassium Sorbate

PURPOSE

Purpose: Sunscreen

CAUTION

CAUTION: 1. Discontinue use and consult a doctor when - your skin irritates, swells, itches, shows spots on areas applied - your skin reacts similarly with above when exposed to sunlight 2. Avoid applying on wounded, irritated, troubled areas 3. After the use - keep the cap closed - keep it out of children's reach - keep it away from expose to sunlight, high and low temperatures

DESCRIPTION

INSTRUCTIONS: Layering Cushion CC covers face moisture as if it has done treatment. 3CE Tinted Moisture Cushion CC creates a moisture layer with a hydrating complex for dewy radiance.

Directions: Take a small amount with the Ruby Cell Puff and spread evenly over face. Please make sure to close the lid after use.